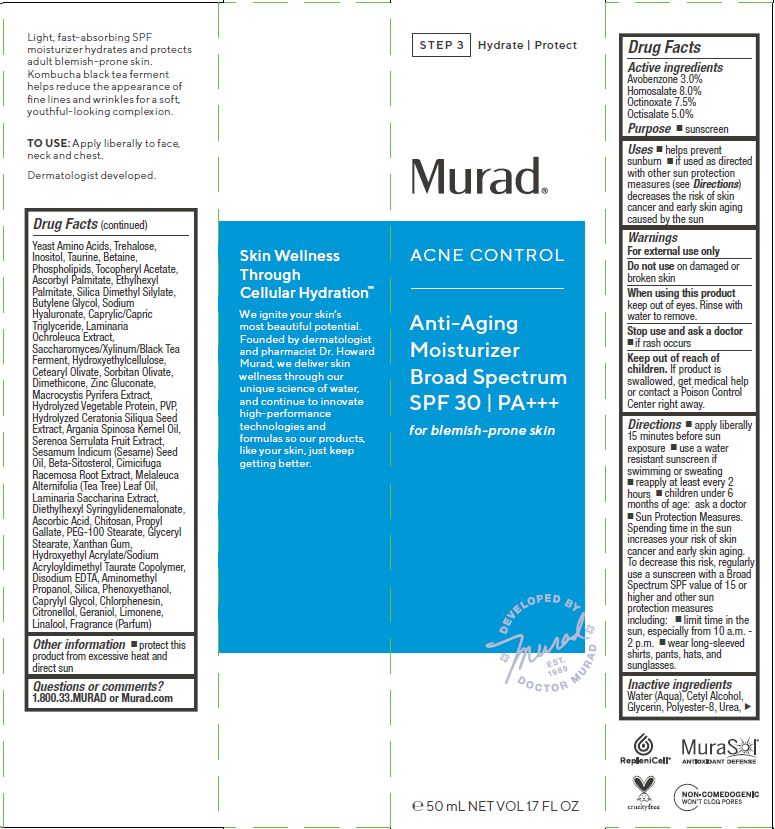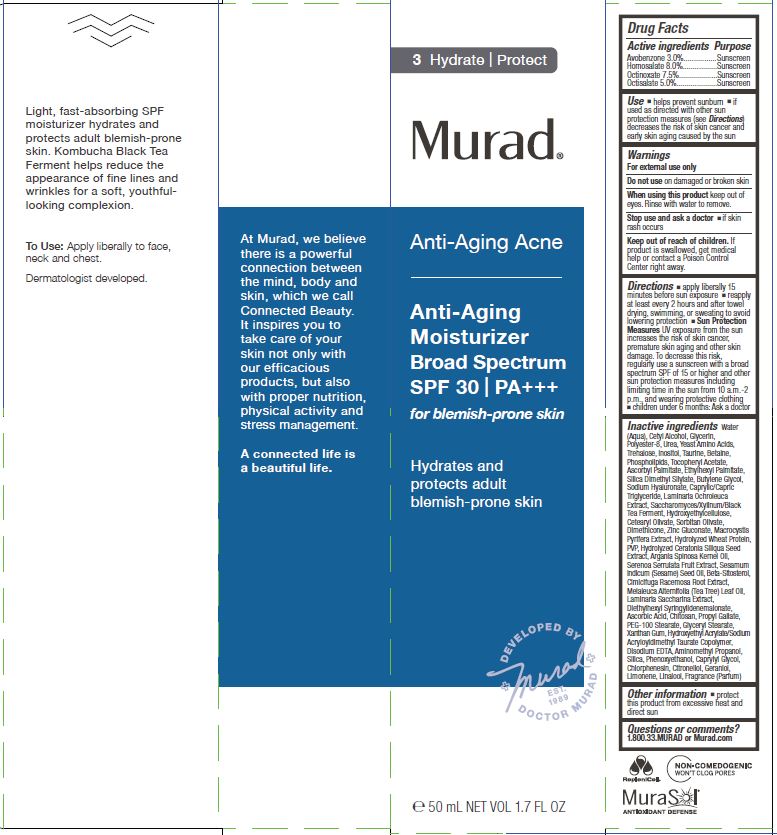 DRUG LABEL: MURAD - ANTI-AGING MOISTURIZER 
NDC: 70381-108 | Form: CREAM
Manufacturer: Murad, LLC
Category: otc | Type: HUMAN OTC DRUG LABEL
Date: 20210129

ACTIVE INGREDIENTS: AVOBENZONE 3 g/100 mL; HOMOSALATE 8 g/100 mL; OCTINOXATE 7.5 g/100 mL; OCTISALATE 5 g/100 mL
INACTIVE INGREDIENTS: WATER; CETYL ALCOHOL; GLYCERIN; POLYESTER-8 (1400 MW, CYANODIPHENYLPROPENOYL CAPPED); UREA; YEAST, UNSPECIFIED; TREHALOSE; INOSITOL; TAURINE; BETAINE; OMEGA-3 FATTY ACIDS; .ALPHA.-TOCOPHEROL ACETATE; VITAMIN A PALMITATE; ETHYLHEXYL PALMITATE; SILICA DIMETHYL SILYLATE; BUTYLENE GLYCOL; HYALURONATE SODIUM; MEDIUM-CHAIN TRIGLYCERIDES; LAMINARIA OCHROLEUCA; SACCHAROMYCES LYSATE; HYDROXYETHYL CELLULOSE (100 MPA.S AT 2%); CETEARYL OLIVATE; SORBITAN OLIVATE; DIMETHICONE; ZINC GLUCONATE; MACROCYSTIS PYRIFERA; HYDROLYZED SOY PROTEIN (ENZYMATIC; 2000 MW); POVIDONE, UNSPECIFIED; CAROB; ARGAN OIL; SAW PALMETTO; SESAME OIL; .BETA.-SITOSTEROL; BLACK COHOSH; TEA TREE OIL; SACCHARINA LATISSIMA; DIETHYLHEXYL SYRINGYLIDENEMALONATE; ASCORBIC ACID; CHITOSAN LOW MOLECULAR WEIGHT (20-200 MPA.S); PROPYL GALLATE; PEG-100 STEARATE; GLYCERYL MONOSTEARATE; XANTHAN GUM; HYDROXYETHYL ACRYLATE/SODIUM ACRYLOYLDIMETHYL TAURATE COPOLYMER (100000 MPA.S AT 1.5%); EDETATE DISODIUM; AMINOMETHYLPROPANOL; SILICON DIOXIDE; PHENOXYETHANOL; CAPRYLYL GLYCOL; CHLORPHENESIN; .BETA.-CITRONELLOL, (R)-; GERANIOL; LIMONENE, (+)-; LINALOOL, (+)-

MURAD - ANTI-AGING ACNE / ACNE CONTROL - ANTI-AGING MOISTURIZER BROAD SPECTRUM SPF 30

ACTIVE INGREDIENTS

Avobenzone 3.0%

Homosalate 8.0%

Octinoxate 7.5%

Octisalate 5.0%

PURPOSE

SUNSCREEN

USES

- helps prevent sunburn
- if used as directed with other sun protection measures (see Directions) decreases the risk of skin cancer and early skin aging caused by the sun.

WARNINGS

For external use only

Do not use on damaged or broken skin

When using this product keep out of eyes. Rinse with water to remove.

Stop use and ask a doctor

- if skin rash occurs

Keep out of reach of children. If product is swallowed, get medical help or contact a Poison Control Center right away.

DIRECTIONS

- apply liberally 15 minutes before sun exposure
- use a water resistant sunscreen if swimming or sweating
- reapply at least every 2 hours
- Sun Protection Measures.pending time in the sun increases your risk of skin cancer and early skin aging. To decrease this risk, regularly use a sunscreen with a Broad Spectrum SPF value of 15 or higher and other sun protection measures including:
- limit time in the sun, especially from 10 a.m. - 2 p.m.
- wear long-sleeved shirts, pants, hats, and sunglasses.
- children under 6 months of age: ask a doctor

INACTIVE INGREDIENTS

Water (Aqua), Cetyl Alcohol, Glycerin, Polyester-8, Urea, Yeast Amino Acids, Trehalose, Inositol, Taurine, Betaine, Phospholipids, Tocopheryl Acetate, Ascorbyl Palmitate, Ethylhexyl Palmitate, Silica Dimethyl Silylate, Butylene Glycol, Sodium Hyaluronate, Caprylic/Capric Triglyceride, Laminaria Ochroleuca Extract, Saccharomyces/Xylinum/Black Tea Ferment, Hydroxyethylcellulose, Cetearyl Olivate, Sorbitan Olivate, Dimethicone, Zinc Gluconate, Macrocystis Pyrifera Extract, Hydrolyzed Vegetable Protein, PVP, Hydrolyzed Ceratonia Siliqua Seed Extract, Argania Spinosa Kernel Oil, Serenoa Serrulata Fruit Extract, Sesamum Indicum (Sesame) Seed Oil, Beta-Sitosterol, Cimicifuga Racemosa Root Extract, Melaleuca Alternifolia (Tea Tree) Leaf Oil, Laminaria Saccharina Extract, Diethylhexyl Syringylidenemalonate, Ascorbic Acid, Chitosan, Propyl Gallate, PEG-100 Stearate, Glyceryl Stearate, Xanthan Gum, Hydroxyethyl Acrylate/Sodium Acryloyldimethyl Taurate Copolymer, Disodium EDTA, Aminomethyl Propanol, Silica, Phenoxyethanol, Caprylyl Glycol, Chlorphenesin, Citronellol, Geraniol, Limonene, Linalool, Fragrance (Parfum)

OTHER INFORMATION

- protect this product from excessive heat and direct sun

QUESTIONS OR COMMENTS?

1.800.33.MURAD or Murad.com